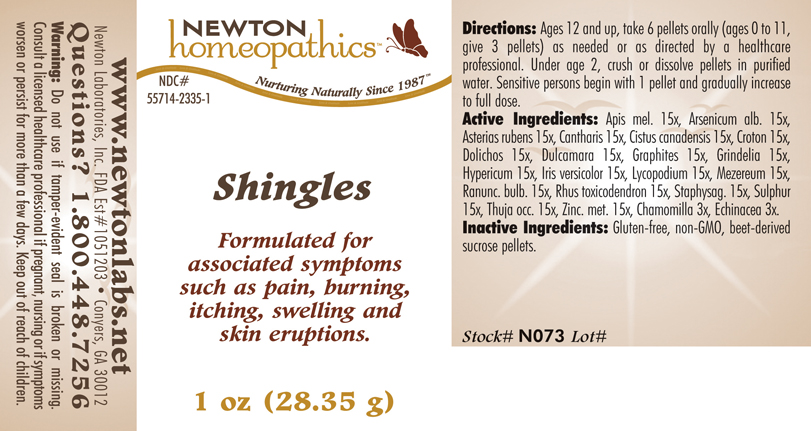 DRUG LABEL: Shingles 
NDC: 55714-2335 | Form: PELLET
Manufacturer: Newton Laboratories, Inc.
Category: homeopathic | Type: HUMAN OTC DRUG LABEL
Date: 20110301

ACTIVE INGREDIENTS: Apis Mellifera 15 [hp_X]/1 g; Arsenic Trioxide 15 [hp_X]/1 g; Asterias Rubens 15 [hp_X]/1 g; Lytta Vesicatoria 15 [hp_X]/1 g; Helianthemum Canadense 15 [hp_X]/1 g; Croton Tiglium Seed 15 [hp_X]/1 g; Mucuna Pruriens Fruit Trichome 15 [hp_X]/1 g; Solanum Dulcamara Top 15 [hp_X]/1 g; Graphite 15 [hp_X]/1 g; Grindelia Hirsutula Flowering Top 15 [hp_X]/1 g; Hypericum Perforatum 15 [hp_X]/1 g; Iris Versicolor Root 15 [hp_X]/1 g; Lycopodium Clavatum Spore 15 [hp_X]/1 g; Daphne Mezereum Bark 15 [hp_X]/1 g; Ranunculus Bulbosus 15 [hp_X]/1 g; Toxicodendron Pubescens Leaf 15 [hp_X]/1 g; Delphinium Staphisagria Seed 15 [hp_X]/1 g; Sulfur 15 [hp_X]/1 g; Thuja Occidentalis Leafy Twig 15 [hp_X]/1 g; Zinc 15 [hp_X]/1 g; Matricaria Recutita 3 [hp_X]/1 g; Echinacea, Unspecified 3 [hp_X]/1 g
INACTIVE INGREDIENTS: Sucrose

Shingles

INDICATIONS & USAGE SECTION

Shingles Formulated for associated symptoms such as pain, burning, itching, swelling and skin eruptions.

DOSAGE & ADMINISTRATION SECTION

Directions: Ages 12 and up, take 6 pellets orally (ages 0 to 11, give 3 pellets) as needed or as directed by a healthcare professional. Under age 2, crush or dissolve pellets in purified water. Sensitive persons begin with 1 pellet and gradually increase to full dose.

OTC - ACTIVE INGREDIENT SECTION

Apis mel. 15x, Arsenicum alb. 15x, Asterias rubens 15x, Cantharis 15x, Cistus canadensis 15x, Croton 15x ,Dolichos 15x, Dulcamara 15x, Graphites 15x, Grindelia 15x, Hypericum 15x, Iris versicolor 15x, Lycopodium 15x, Mezereum 15x, Ranunc. bulb. 15x, Rhus toxicodendron 15x, Staphysag. 15x, Sulphur 15x, Thuja occ. 15x, Zinc. met. 15x, Chamomilla 3x, Echinacea 3x.

OTC - PURPOSE SECTION

Formulated for associated symptoms such as pain, burning, itching, swelling and skin eruptions.

INACTIVE INGREDIENT SECTION

Inactive Ingredients: Gluten-free, non-GMO, beet-derived sucrose pellets.

QUESTIONS SECTION

www.newtonlabs.net Newton Laboratories, Inc. FDA Est # 1051203 - Conyers, GA 30012
Questions? 1.800.448.7256

WARNINGS SECTION

Warning: Do not use if tamper - evident seal is broken or missing. Consult a licensed healthcare professional if pregnant, nursing or if symptoms worsen or persist for more than a few days. Keep out of reach of children.

OTC - PREGNANCY OR BREAST FEEDING SECTION

Consult a licensed healthcare professional if pregnant, nursing or if symptoms worsen or persist for more than a few days.

OTC - KEEP OUT OF REACH OF CHILDREN SECTION

Keep out of reach of children.